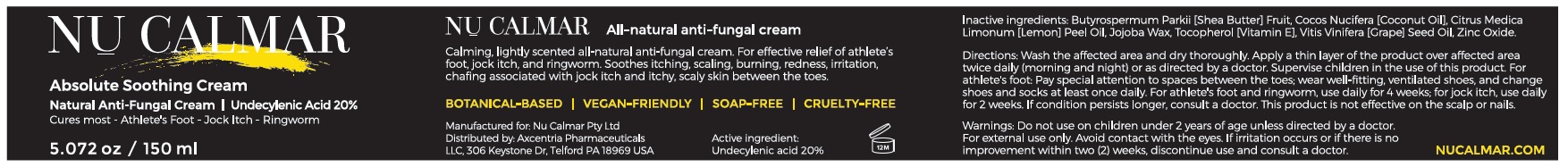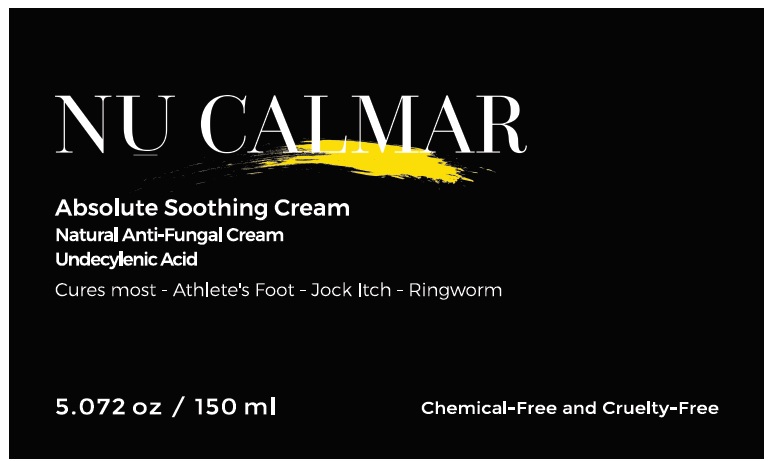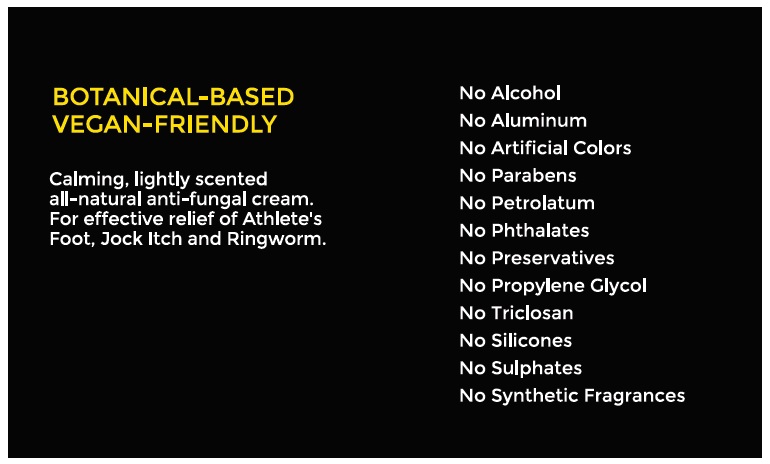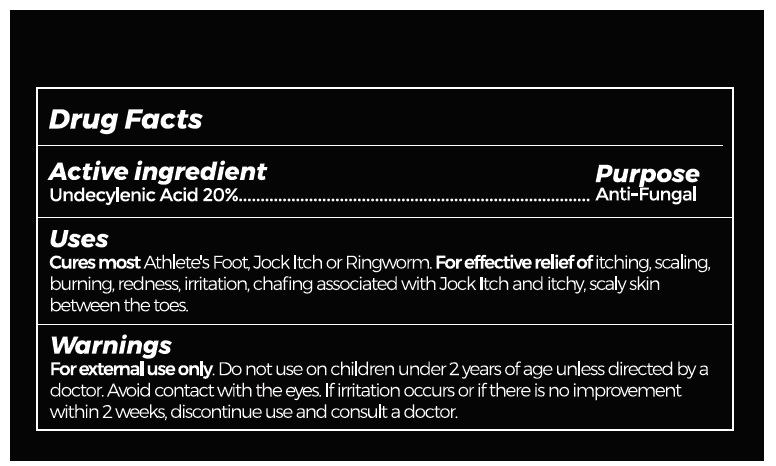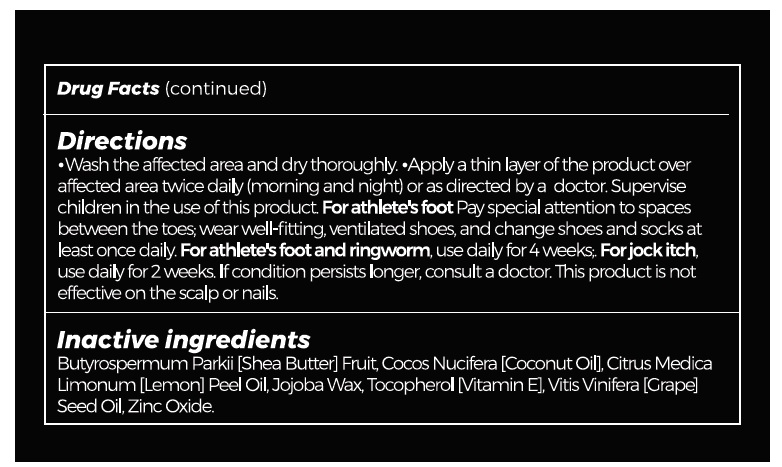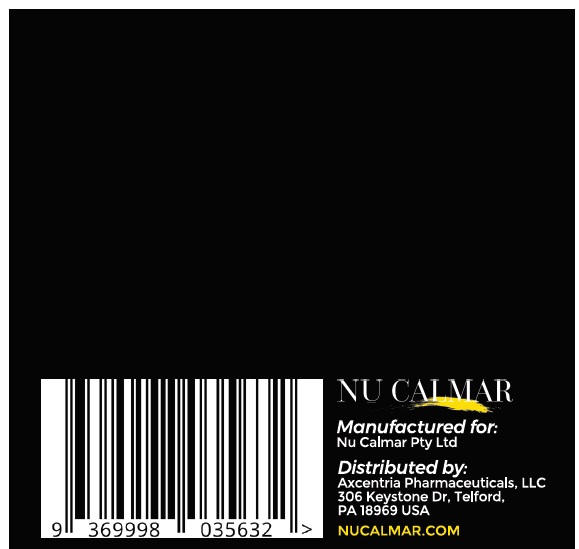 DRUG LABEL: NU CALMAR
NDC: 73464-001 | Form: CREAM
Manufacturer: Nu Calmar Pty Ltd
Category: otc | Type: HUMAN OTC DRUG LABEL
Date: 20221104

ACTIVE INGREDIENTS: UNDECYLENIC ACID 200 mg/1 mL
INACTIVE INGREDIENTS: SHEA BUTTER; COCONUT OIL; LEMON OIL; HYDROGENATED JOJOBA OIL, RANDOMIZED; TOCOPHEROL; GRAPE SEED OIL; ZINC OXIDE; GLYCERIN

DRUG FACTS Active Ingredient

Undecylenic Acid 20%

Purpose

Anti-fungal

Uses:

Cures most Athlete's Foot, Jock Itch or Ringworm. For effective relief of itching, scaling, burning, redness, irritation, chafing associated with jock itch and itchy scaly skin between the toes.

Warning:

For external use only. Do not use on children under 2 years of age unless directed by a doctor. Avoid contact with the eyes. If irritation occurs or if there is no improvement within 2 weeks, discontinue use and consult a doctor.

Directions:

Wash the affected area and dry thoroughly. Apply a thin layer of the product over affected area twice daily (morning and night), or as directed by a doctor. Supervise children in the use of this product. For athlete's foot. Pay special attention to spaces between the toes; wear well-fitting, ventilated shoes, and change shoes and socks at least once daily. For athlete's foot and ringworm, use daily for 4 weeks. For jock itch, use daily for 2 weeks. If condition persists longer, consult a doctor. This product is not effective on the scalp or nails.

Inactive ingredients:

Shea butter, Coconut Oil, Lemon Oil, Jojoba wax, Tocopherol, Grape Seed Oil, Zinc Oxide, Glycerin (Vegetable)